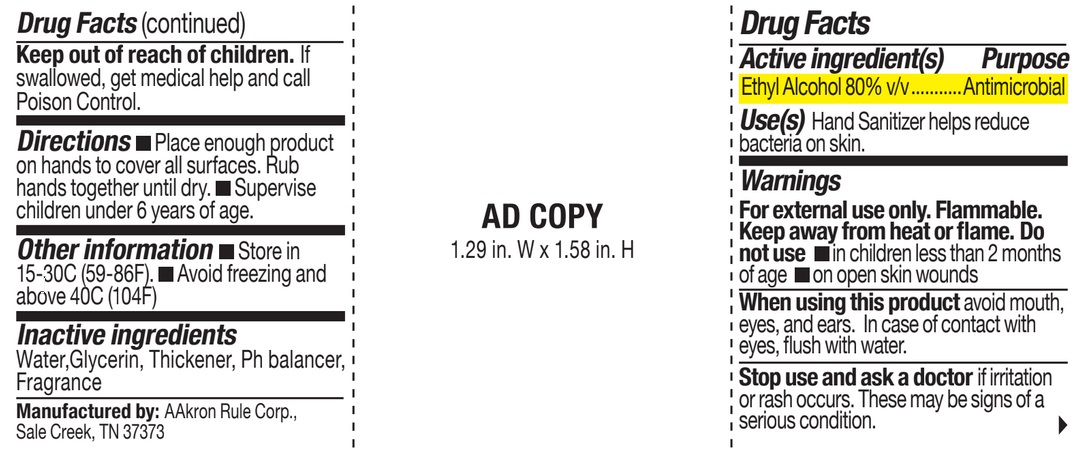 DRUG LABEL: Sanitizer
NDC: 69394-002 | Form: GEL
Manufacturer: AAkron Rule Corporation
Category: otc | Type: HUMAN OTC DRUG LABEL
Date: 20220725

ACTIVE INGREDIENTS: ALCOHOL 80 mL/100 mL
INACTIVE INGREDIENTS: GLYCERIN; WATER; AMINOMETHYLPROPANOL; CETEARETH-5; CYCLOHEXANE

Active Ingredient

Ethyl Alcohol 80% v/v

Purpose

Antimicrobial

Use

Hand Sanitizer to help reduce bacteria on skin.

Warnings

For external use only.

Flammable. Keep away from heat or flame.

Do not use

- in children less than 2 months of age
- on open skin wounds

When using this product avoid mouth, eyes and ears. In case of contact with eyes, flush with water.
Stop use and ask a doctor if irritation or rash occurs. These may be signs of a serious condition.

Keep out of reach of children. If swallowed, get medical help and call Poison Control.

Directions

- Place enough product on hands to cover all surfaces. Rub hands together until dry.
- Supervise children under 6 years of age.

Other information

- Store in 15-30C (59-86F)
- Avoid freezing and above 40C (104F)

Inactive ingredients

Water,Glycerin, Thickener, Ph balancer, Fragrance